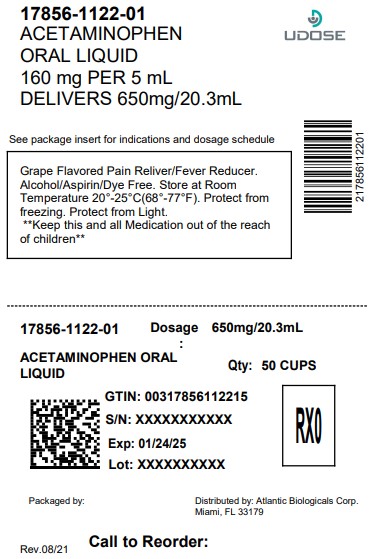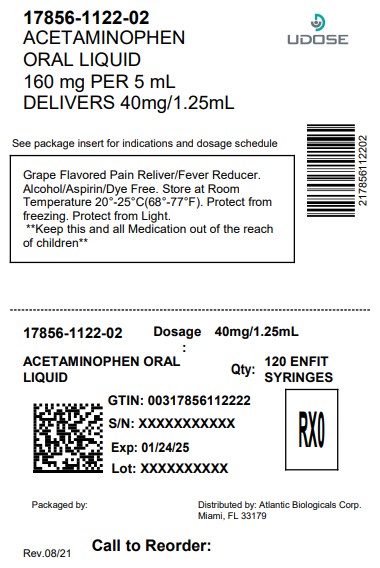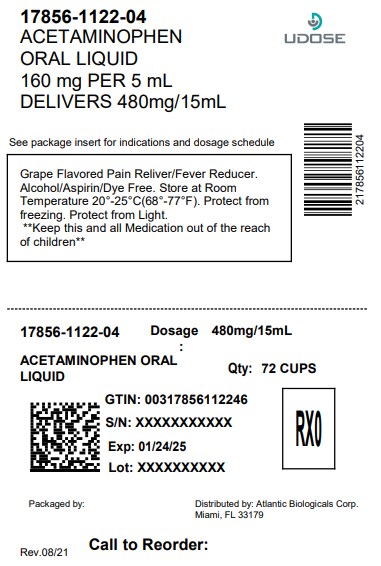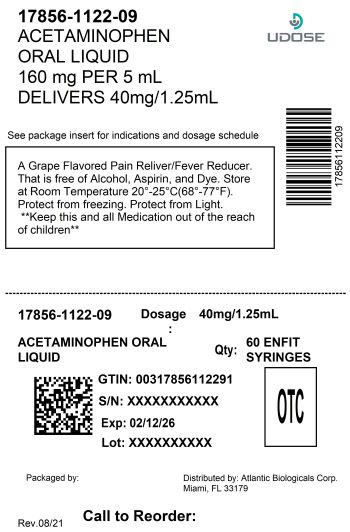 DRUG LABEL: MAX relief junior Grape
NDC: 17856-1122 | Form: LIQUID
Manufacturer: ATLANTIC BIOLOGICALS CORP.
Category: otc | Type: HUMAN OTC DRUG LABEL
Date: 20260213

ACTIVE INGREDIENTS: ACETAMINOPHEN 160 mg/5 mL
INACTIVE INGREDIENTS: ANHYDROUS CITRIC ACID; GLYCERIN; POLYETHYLENE GLYCOL 400; WATER; SACCHARIN SODIUM; SODIUM BENZOATE; SORBITOL; SODIUM CITRATE; SUCRALOSE

MAX relief junior
Children's Pain Reliever
Acetaminophen Oral Liquid Grape Flavor
160mg per 5mL
Alcohol Free
Aspirin Free

Active Ingredient

Active ingredient(in each 5mL) Purpose
Acetaminophen 160 mg ………………………….........Pain reliever/fever reducer

Uses

temporarily:

- reduces fever

relieves minor aches and pains due to:

- the common cold
- flu
- headache
- sore throat
- toothache

Warnings

Liver Warning: This product contains acetaminophen. Severe liver damage may occur if your child takes:

- more then 5 doses in 24 hours, which is the maximum daily amount
- with other drugs containing acetaminophen

Allergy alert:Acetaminophen may cause severe skin reactions. Symptoms may include:

- skin reddening
- blisters
- rash

If a skin reaction occurs, stop use and seek medical help right away.

Sore throat warning:

if sore throat is severe, persist or more than 2 days, is accompanied or followed by fever, headache, rash, nausea or vomiting, consult a doctor promptly.

Do not use

- with any other drug containing acetaminophen (prescription or nonprescription).
- If you are not sure whether a drug contains acetaminophen, ask a doctor or pharmacist.
- if your child is allergic to acetaminophen or anyof the inactive ingredients in this product.

Ask a doctor or pharmacist before use if the child has

liver disease.

Ask doctor or pharmacist before use if your child is

taking the blood thinning drug warfarin. When using this product do not exceed recommended dose (see overdose warning)

Stop use and ask a doctor if

- pain gets worse or lasts for more then 5 days
- fever gets worse or last for more then 3 days
- new symptoms occur redness or swelling is present. These could be signs of a serious condition.

Overdose warning:

In case of overdose, get medical help to contact Poison Control Center (1-800-222-1222) right away. Quick medical attention is critical even if you do not notice any signs or symptoms.

Directions

- this product does not contain directions or complete warnings for adult use
- shake well before using
- mL = milliliter
- find right dose on chart below. if possible, use weight to dose, otherwise use age
- use only the enclosed dosing cup designed for use with product.
- if needed, repeat dose every 4 hours while symptoms last
- do not give more than 5 times in 24 hours.

Weight (lbs) | Age (yrs.) | Dose (tsp or mL) | Weight (lbs) | Age (yrs.) | Dose (tsp or mL)
under 24 | under 2 | ask a doctor | 48 to 59 | 6 to 8 | 2 tsp or 10 mL
25 to 35 | 2 to 3 | 1 tsp or 5 mL | 60 to 71 | 9 to 10 | 2 1/2 tsp or 12.5 mL
36 to 47 | 4 to 5 | 1 1/2 tsp or 7.5 mL | 72 to 95 | 11 | 3 tsp or 15 mL

Other Information

- Store at room temperature 20°-25°C (68°-77°F). Protect from freezing. Protect from light.

Inactive Ingredients

Anhydrous Citric Acid, Glycerin, Grape Flavor, Polyethylene Glycol 400, Purified Water, Saccharin Sodium, Sodium Benzoate, Sorbitol Solution, Sodium Citrate, Sucralose.

Questions or comments?

call toll-free 1-877-225-6999

Manufactured for:

Akron Pharma, Inc.

Fairfield, NJ 07004

www.akronpharma.com